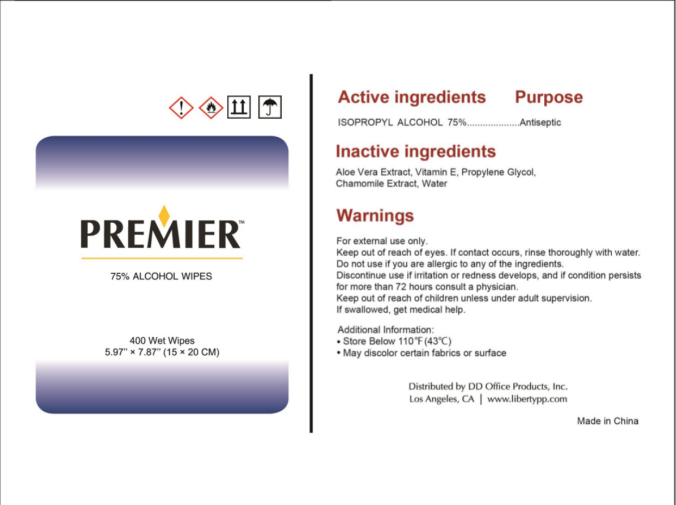 DRUG LABEL: 400 WET WIPES
NDC: 55415-005 | Form: CLOTH
Manufacturer: JIANGSU MEIFAN BIOTECHNOLOGY CO., LTD.
Category: otc | Type: HUMAN OTC DRUG LABEL
Date: 20240322

ACTIVE INGREDIENTS: ISOPROPYL ALCOHOL 1130 g/400 1
INACTIVE INGREDIENTS: ALOE VERA LEAF; WATER; .ALPHA.-TOCOPHEROL; PROPYLENE GLYCOL; CHAMOMILE

55415-05

DOSAGE AND ADMINISTRATION

Do notuse or store near heator open flame.

INACTIVE INGREDIENT

ALOE VERA EXTRACT, VITAMIN E, PROPYLENE GLYCOL, CHAMOMILE EXTRACT, WATER

INDICATIONS AND USAGE

1. Pullout wipe from center of roll
2. Pass through center opening,
3. Next sheet POPS up automatically
To clean; Wipe surface dleanwith this product. Let air dry.

To disinfect: Wipe suyrface; use enough wipes to surface to remain visiblywetfor 3 minutes.

ACTIVE INGREDIENT

ISOPROPYL ALCOHOL

keep out of children

PURPOSE

Disinfection
Sterilization
No Rinseing

WARNINGS

For external use only.Keep out of reach of eyes. If contact occurs. rinse thoroughly with water.